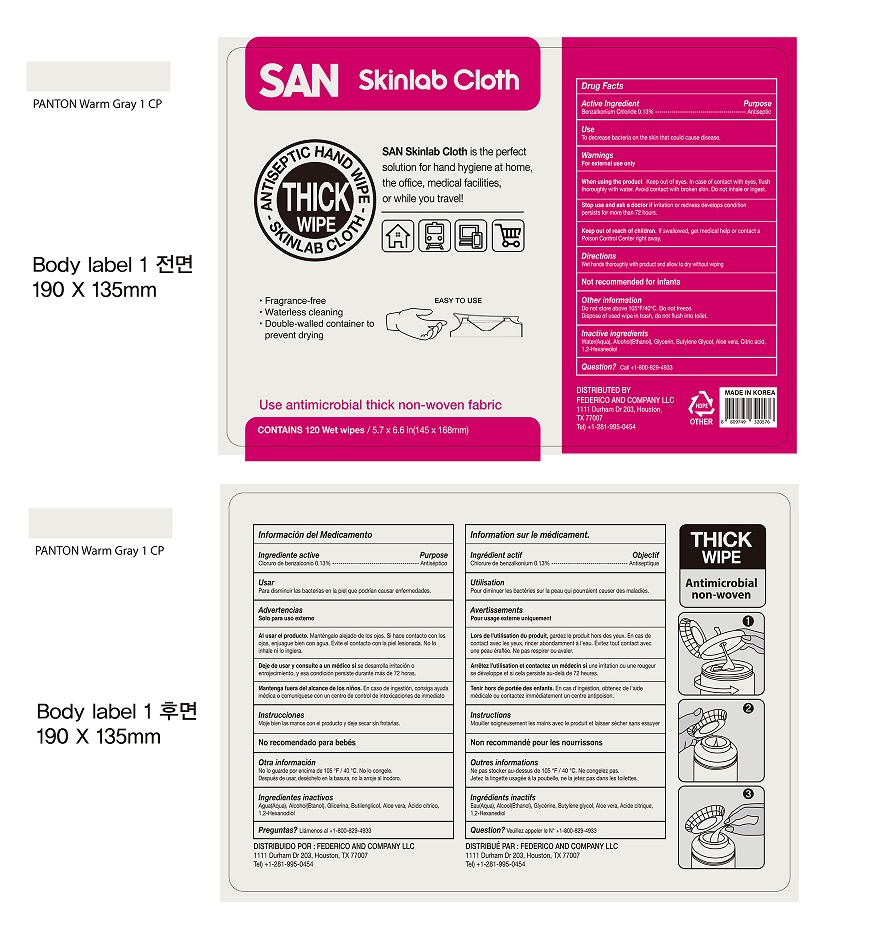 DRUG LABEL: SAN Skinlab Cloth Wet Wipes
NDC: 75214-120 | Form: CLOTH
Manufacturer: HANUL CO.,LTD
Category: otc | Type: HUMAN OTC DRUG LABEL
Date: 20250120

ACTIVE INGREDIENTS: BENZALKONIUM CHLORIDE 0.13 mg/100 mL
INACTIVE INGREDIENTS: ALCOHOL; CITRIC ACID MONOHYDRATE; 1,2-HEXANEDIOL; ALOE VERA LEAF; GLYCERIN; BUTYLENE GLYCOL; WATER

SAN Skinlab Cloth THICK WIPE 120 Wet Wipes

Active Ingredient(s)

Benzalkonium Chloride 0.13%. Purpose: Antiseptic

Purpose

Antiseptic,

Use

to decrease bacteria on the skin that could cause disease

Warnings

For external use only.

WHEN USING

Keep out of eyes, in case of contact with eyes, flush thoroughly with water, Avoid contact with broken skin, Do Not inhale or ingest

Stop use and ask a doctor if irritation or redness developes condition persist for more than 72 hours.

Keep out of reach of children. If swallowed, get medical help or contact a Poison Control Center right away.

Directions

Wet hands thoroughly with product and allow to dry without wiping

Not recommended for infants

Other information

- Do not Store above 105F/40 Degree .Do not Freeze
- Dispose of used wipe in trash, do not flush into toilet

Inactive ingredients

Water (Aqua) , Alcohol (Ethanol). Glycerin,Butylene Glycol, Aloe Vera, Citric Acid, 1,2 hexanediol

Package Label - Principal Display Panel

120 Wet wipes NDC 75214-120-01